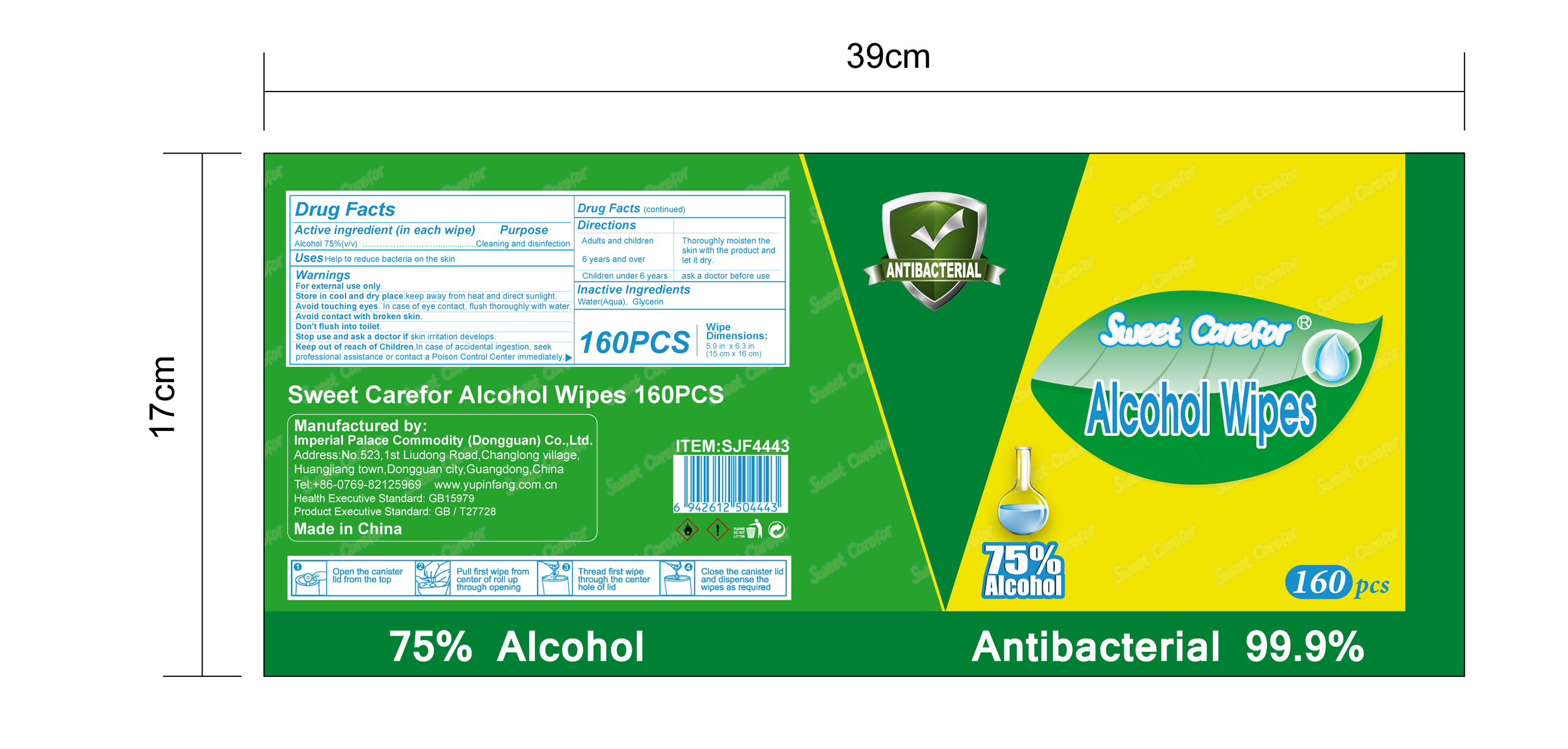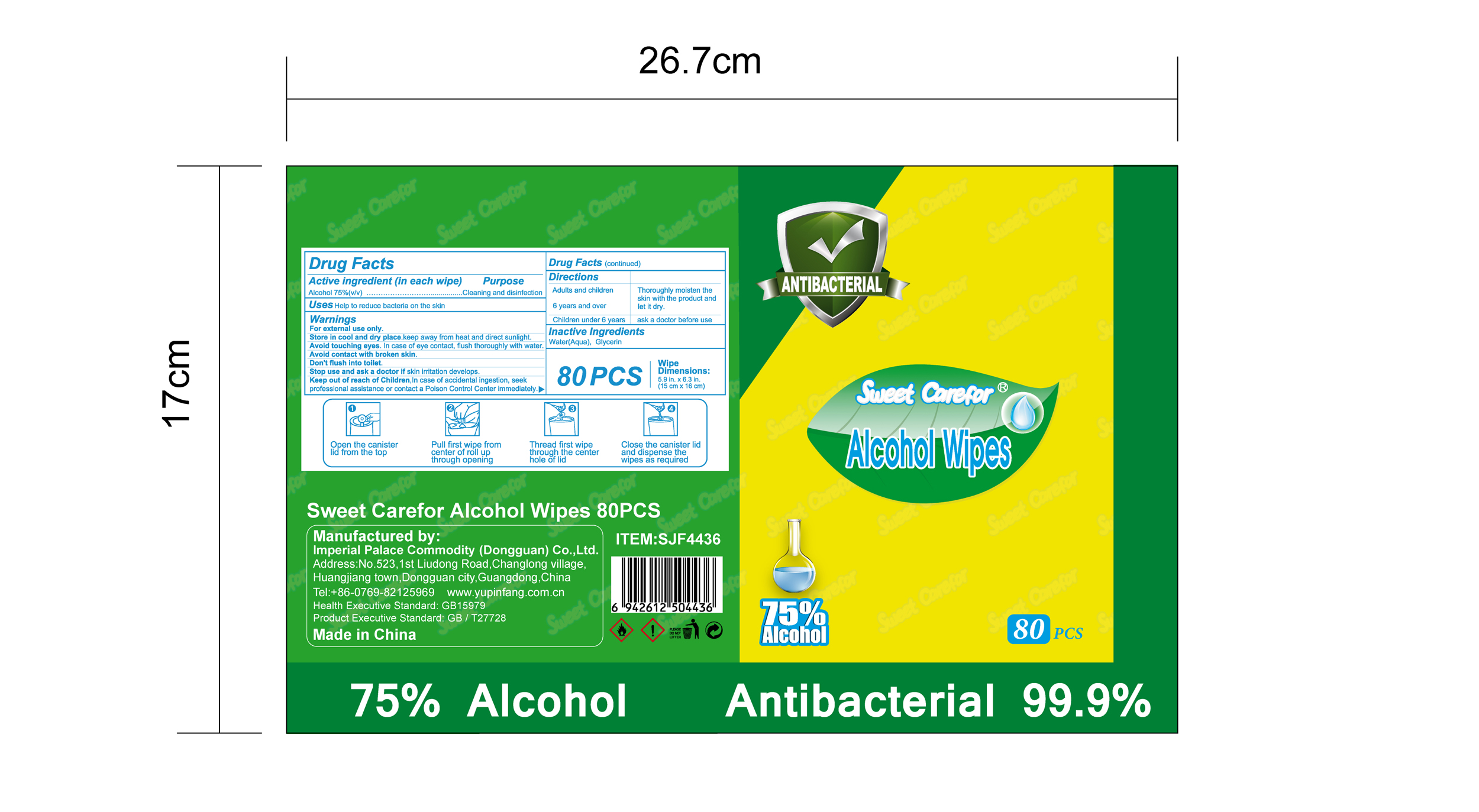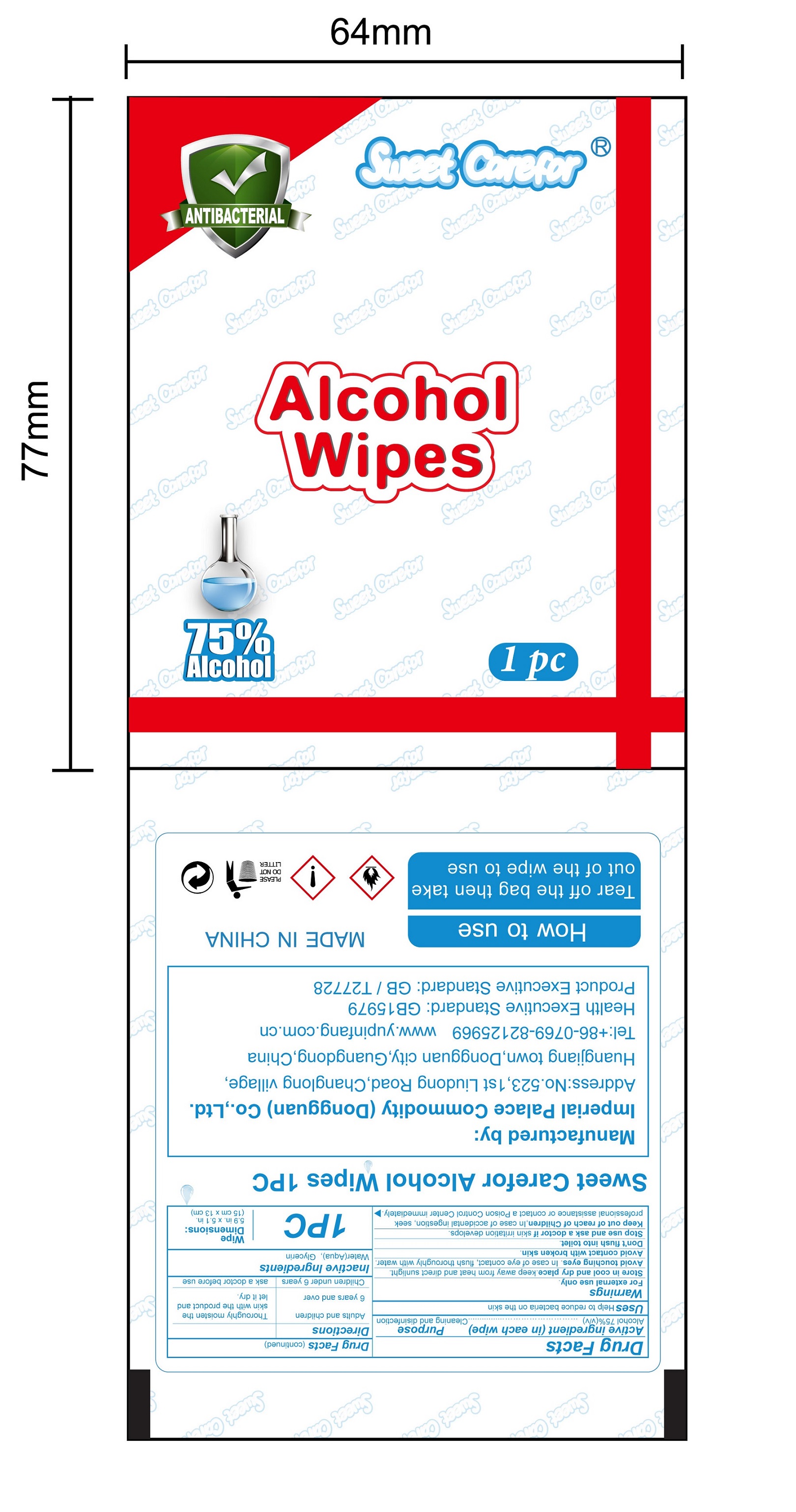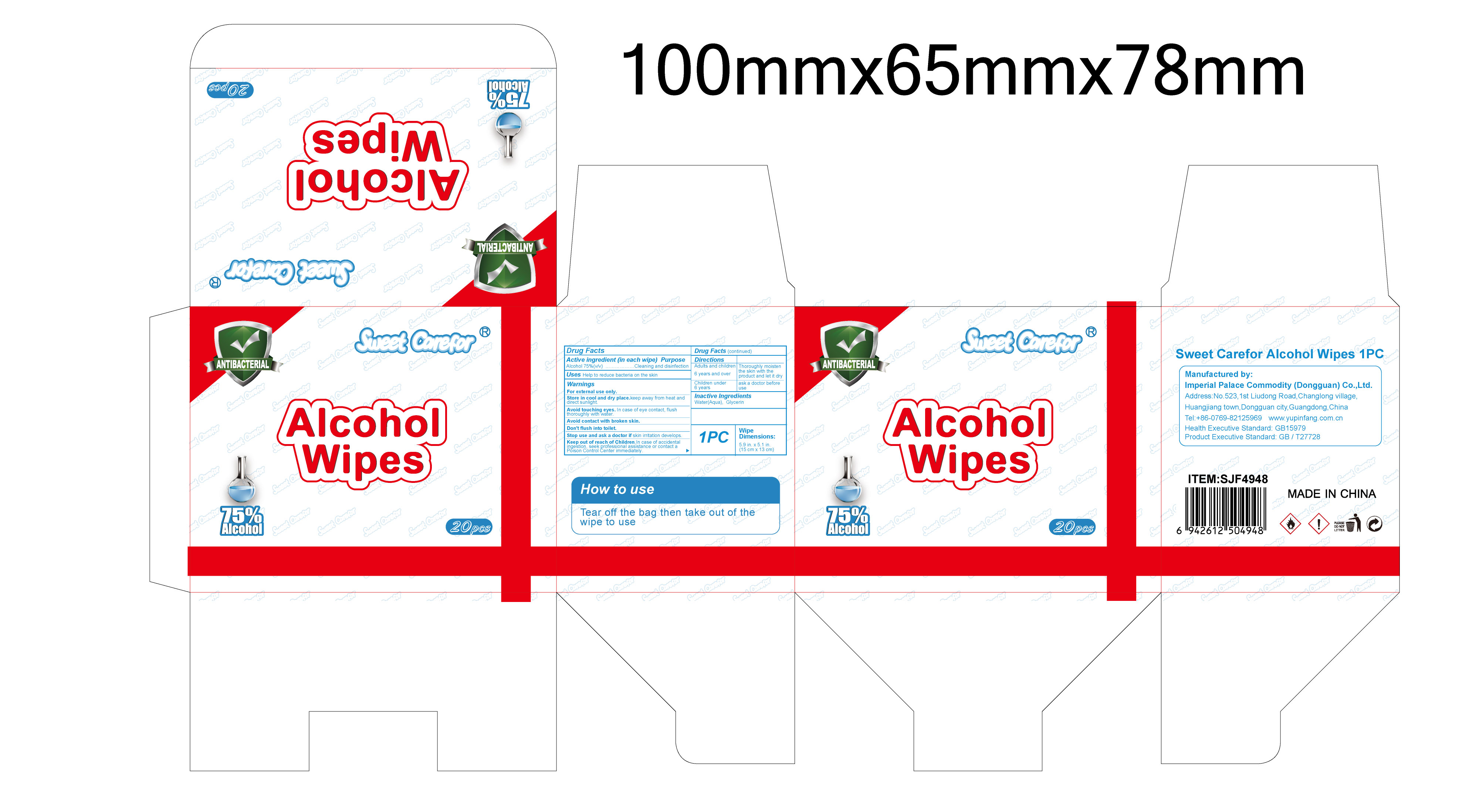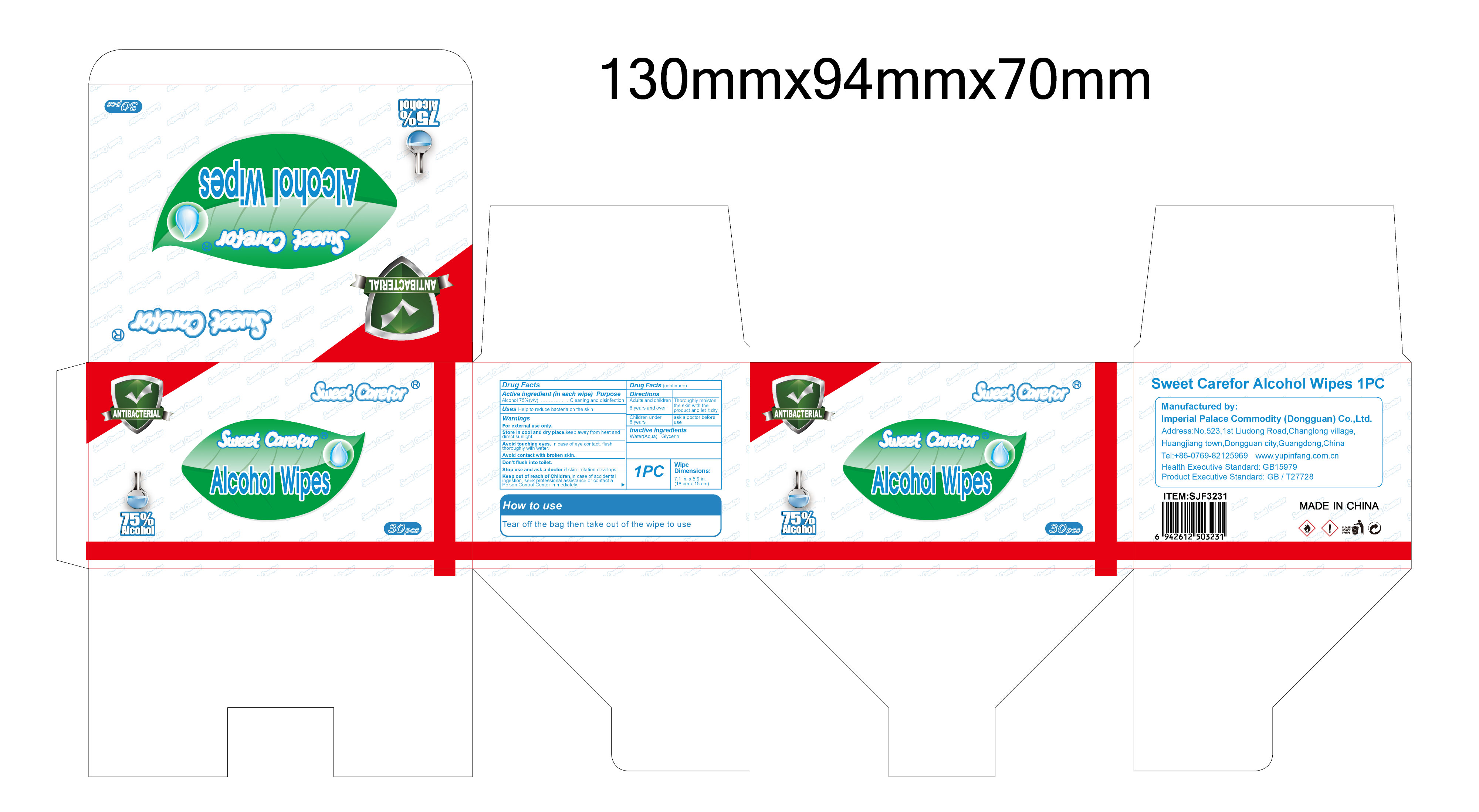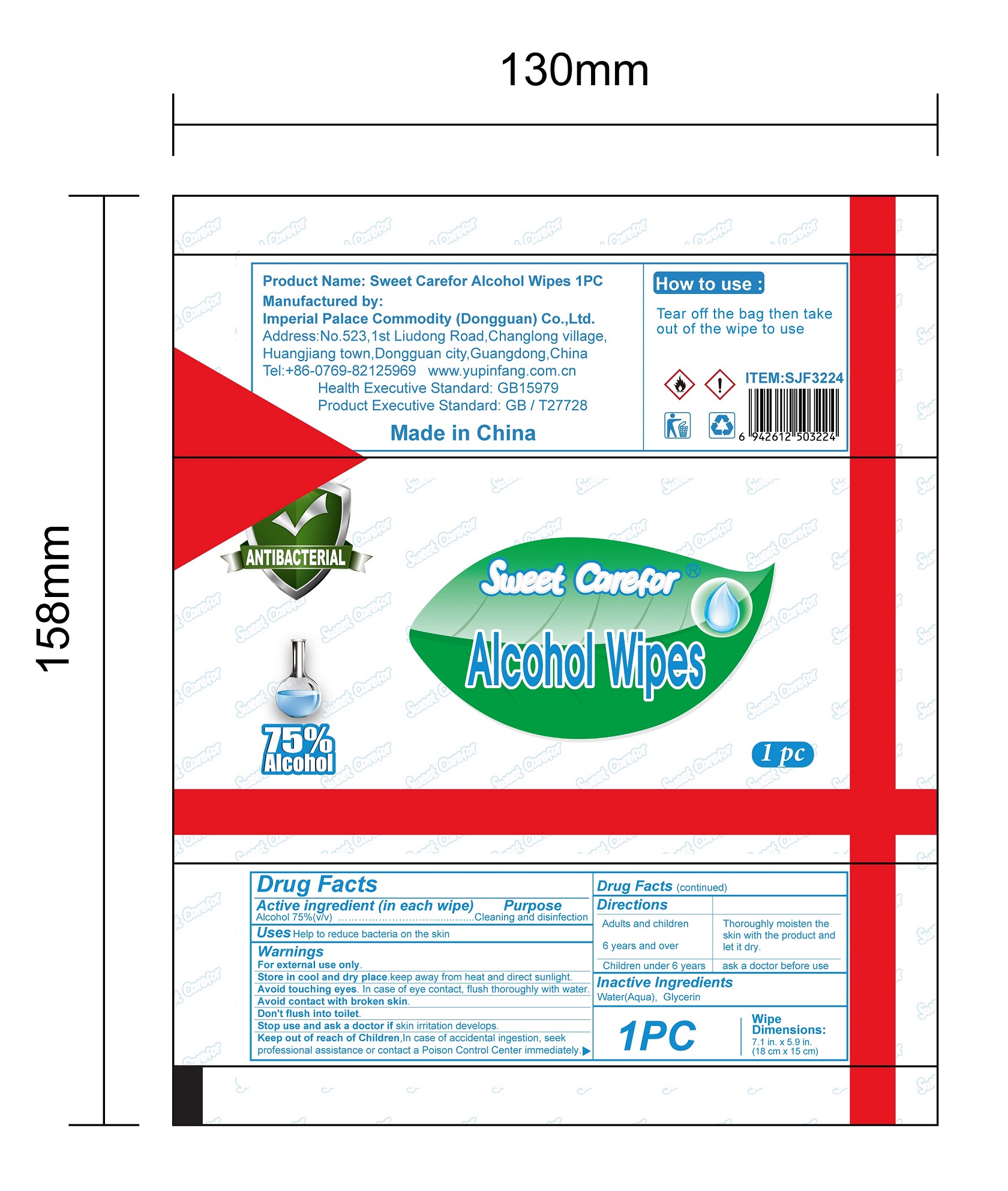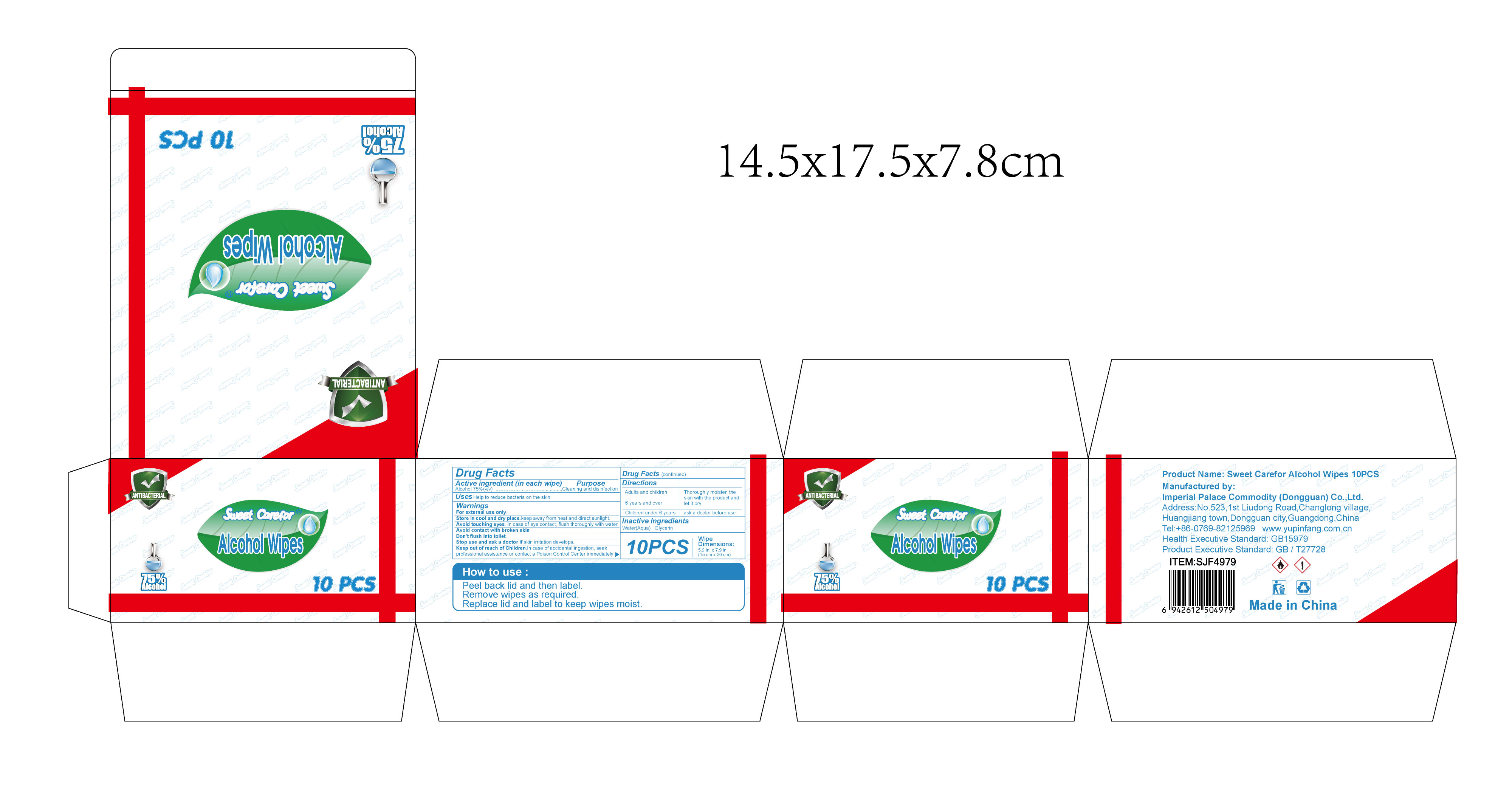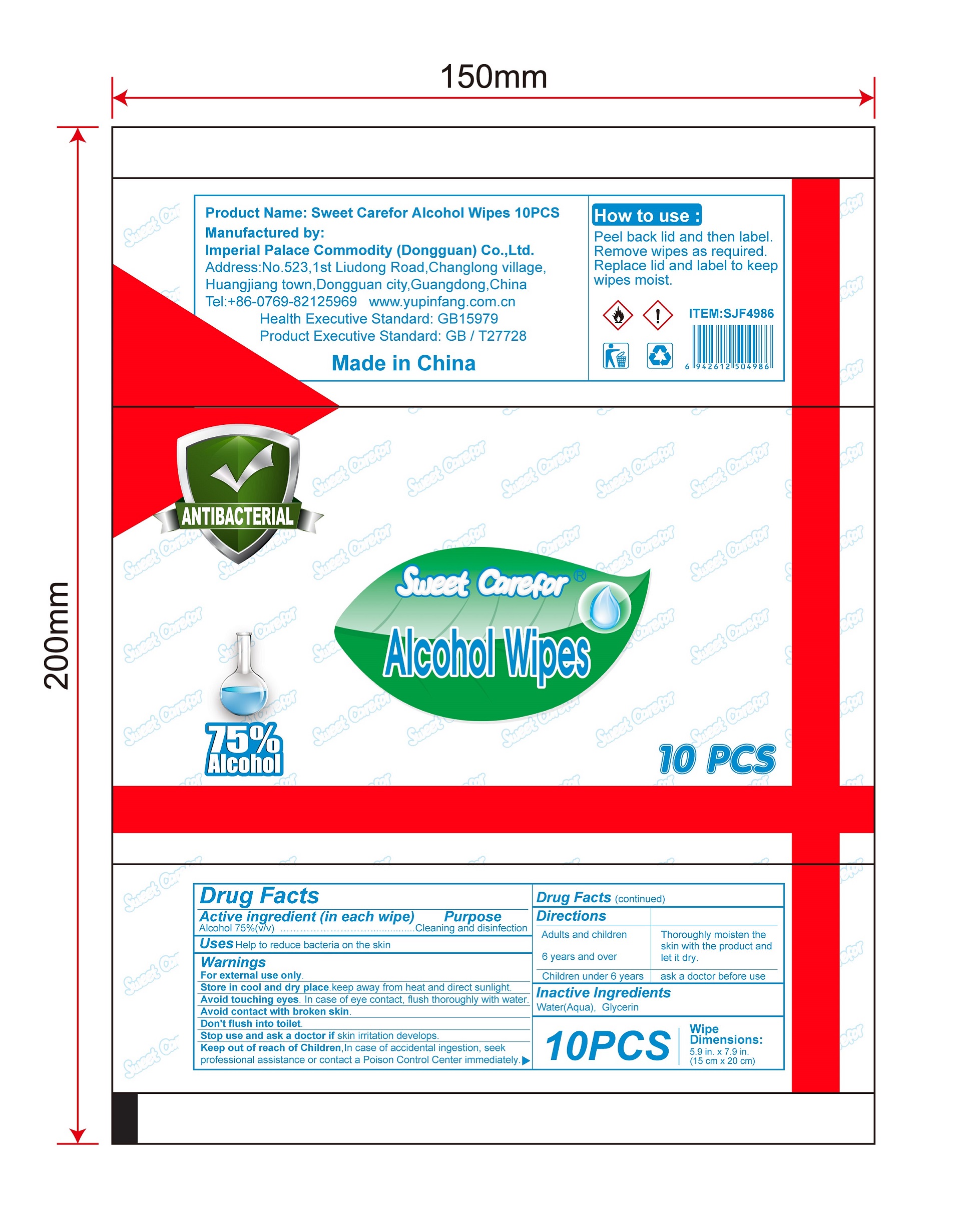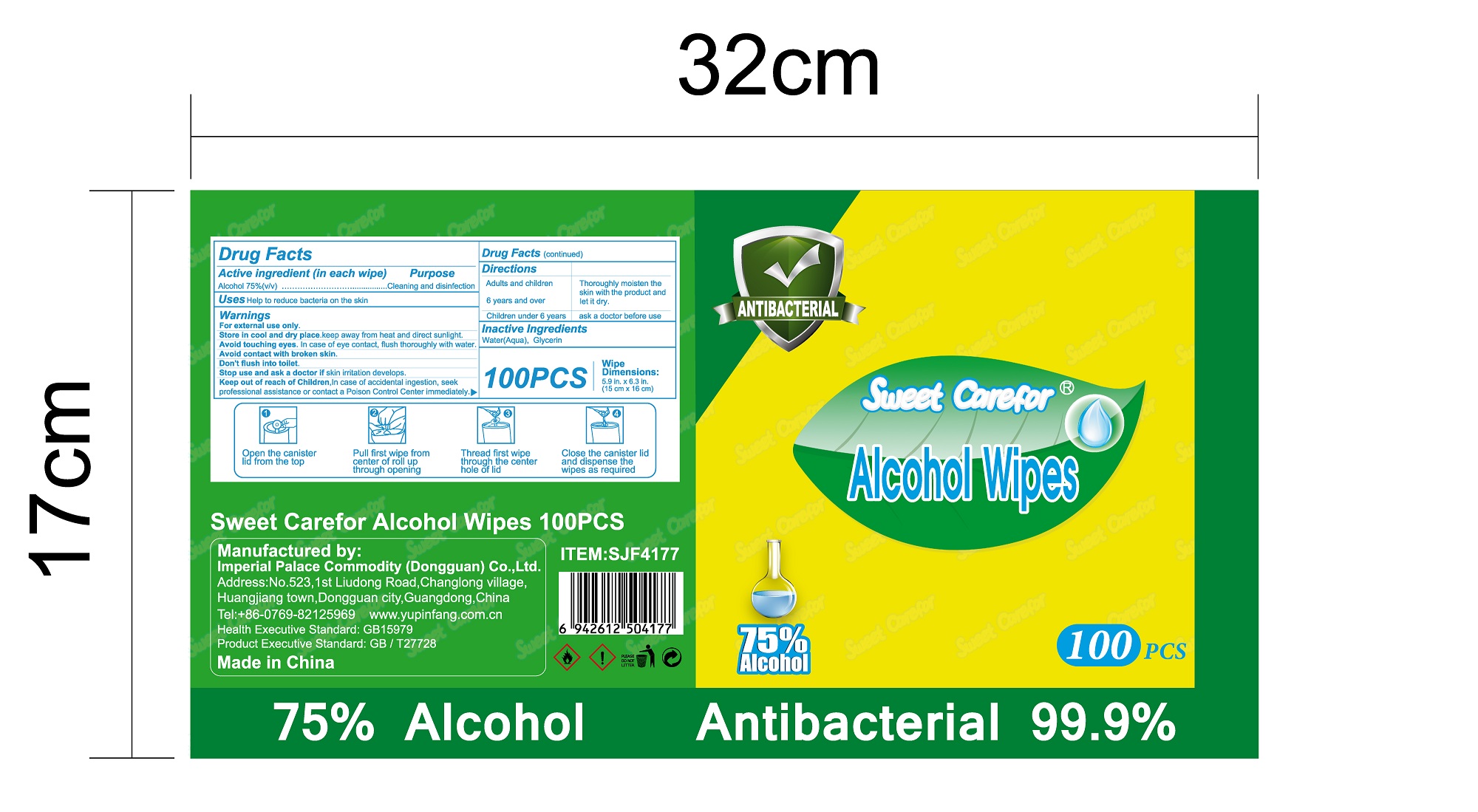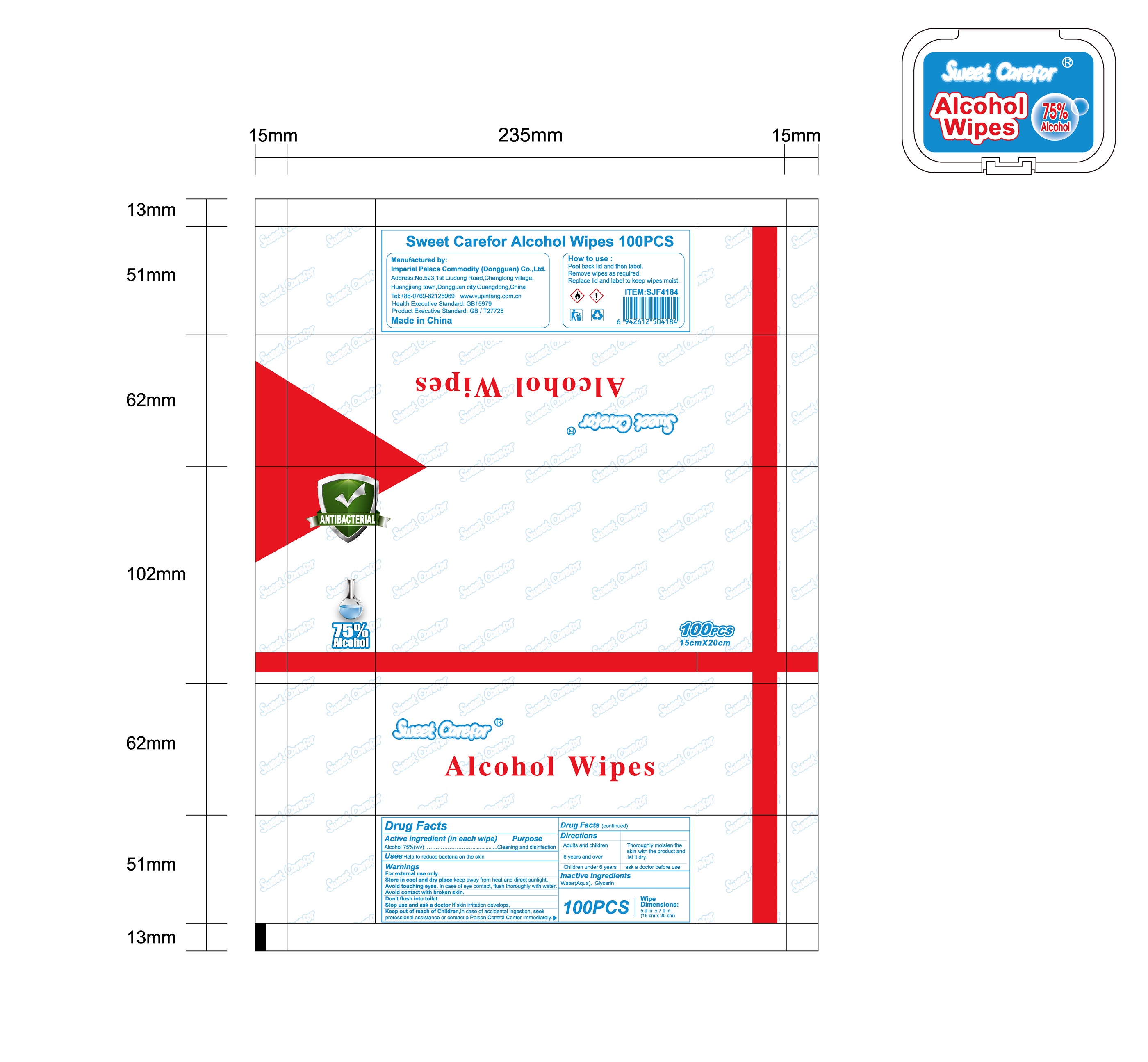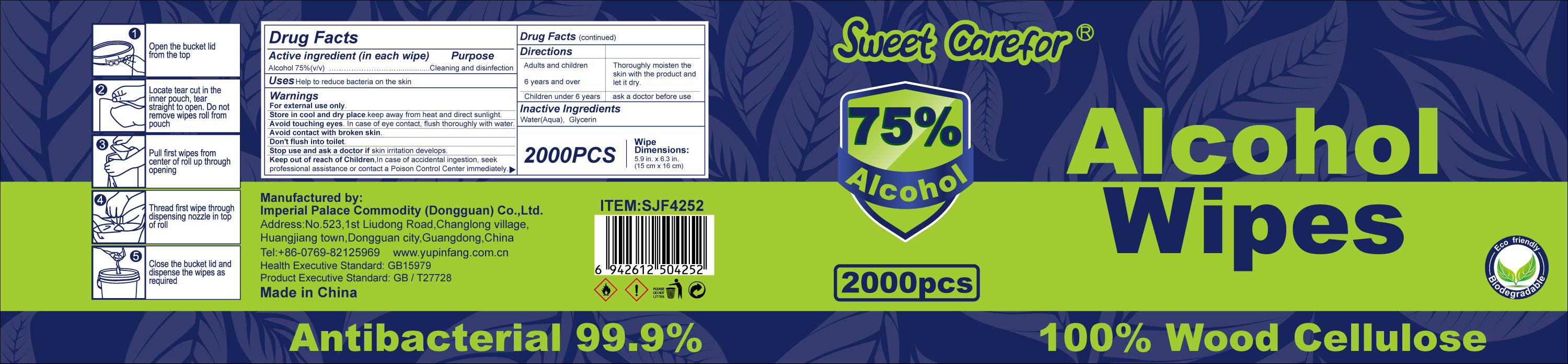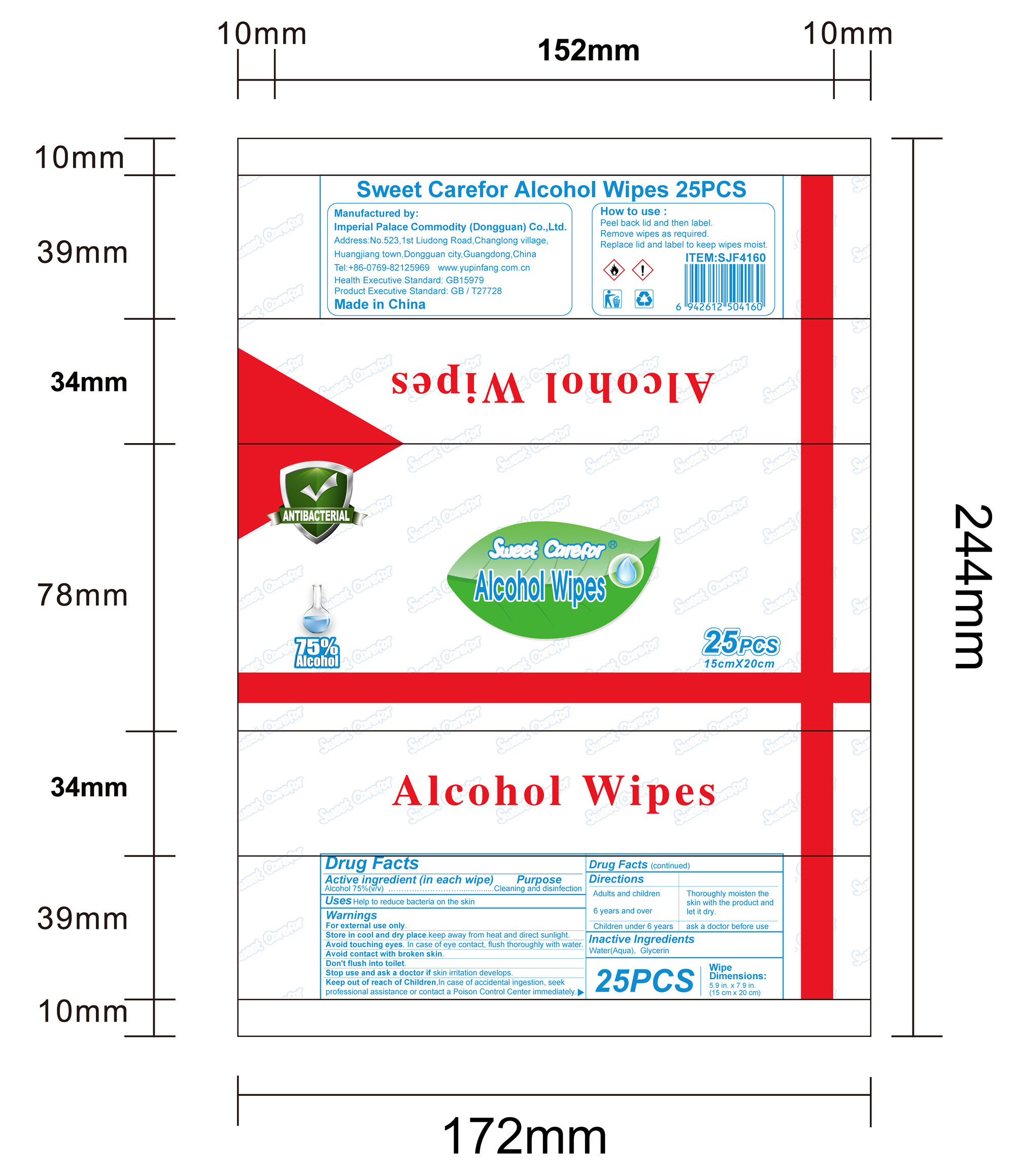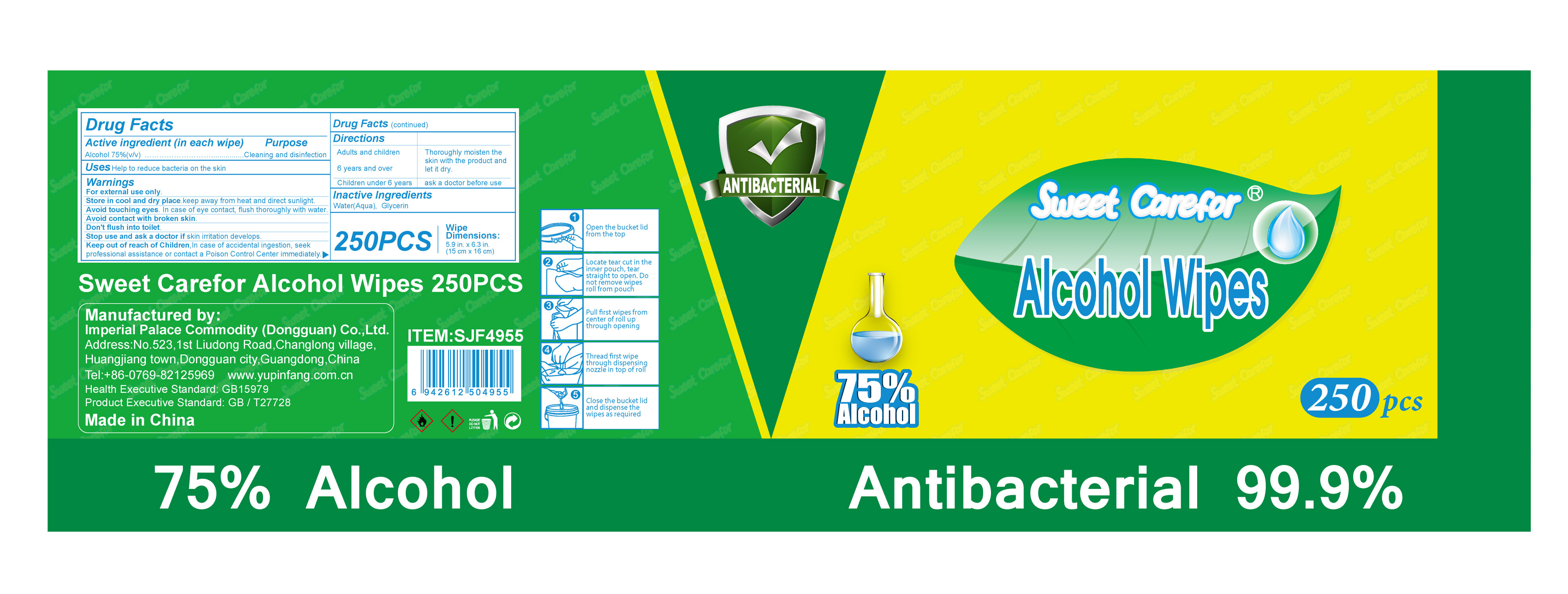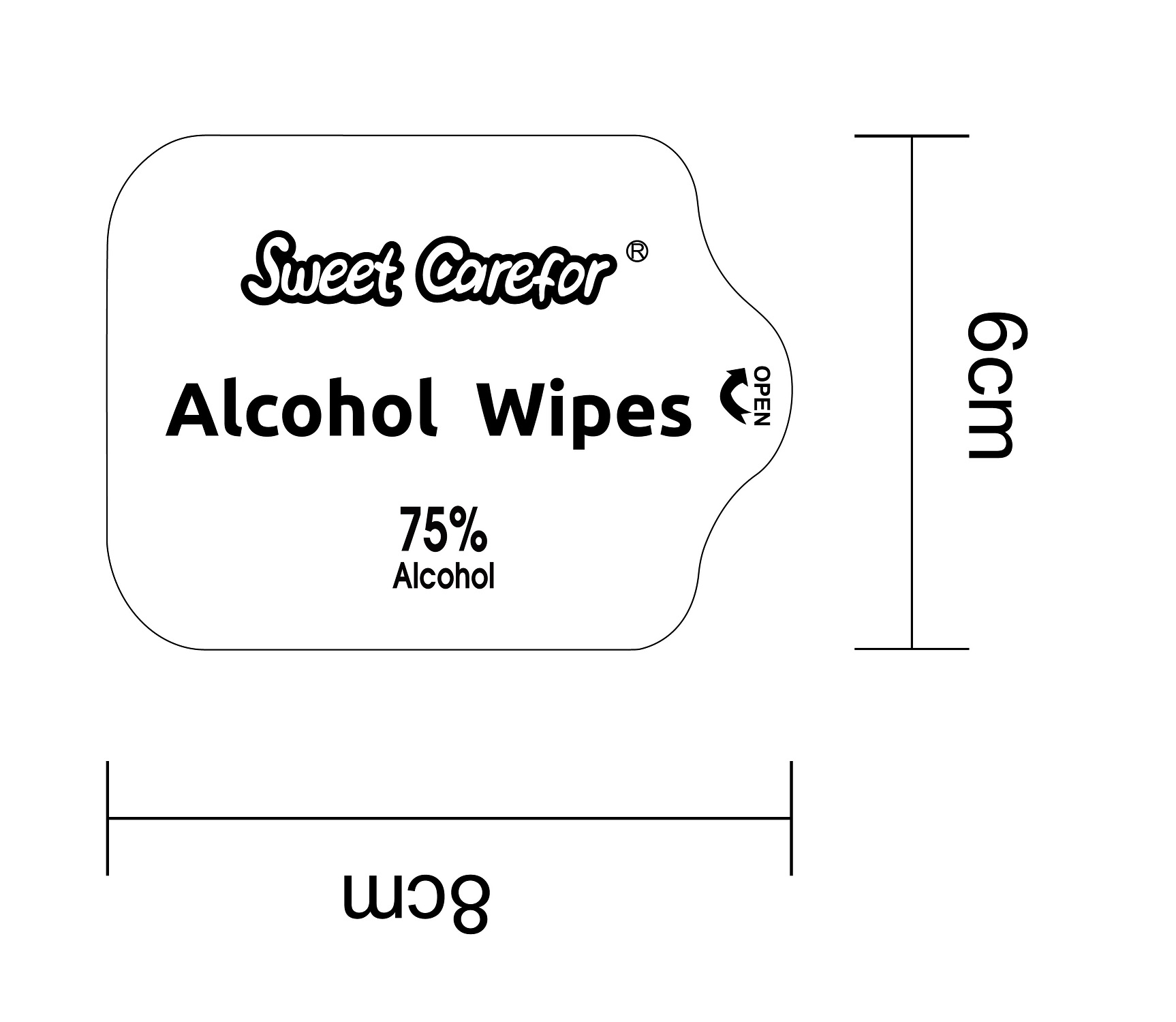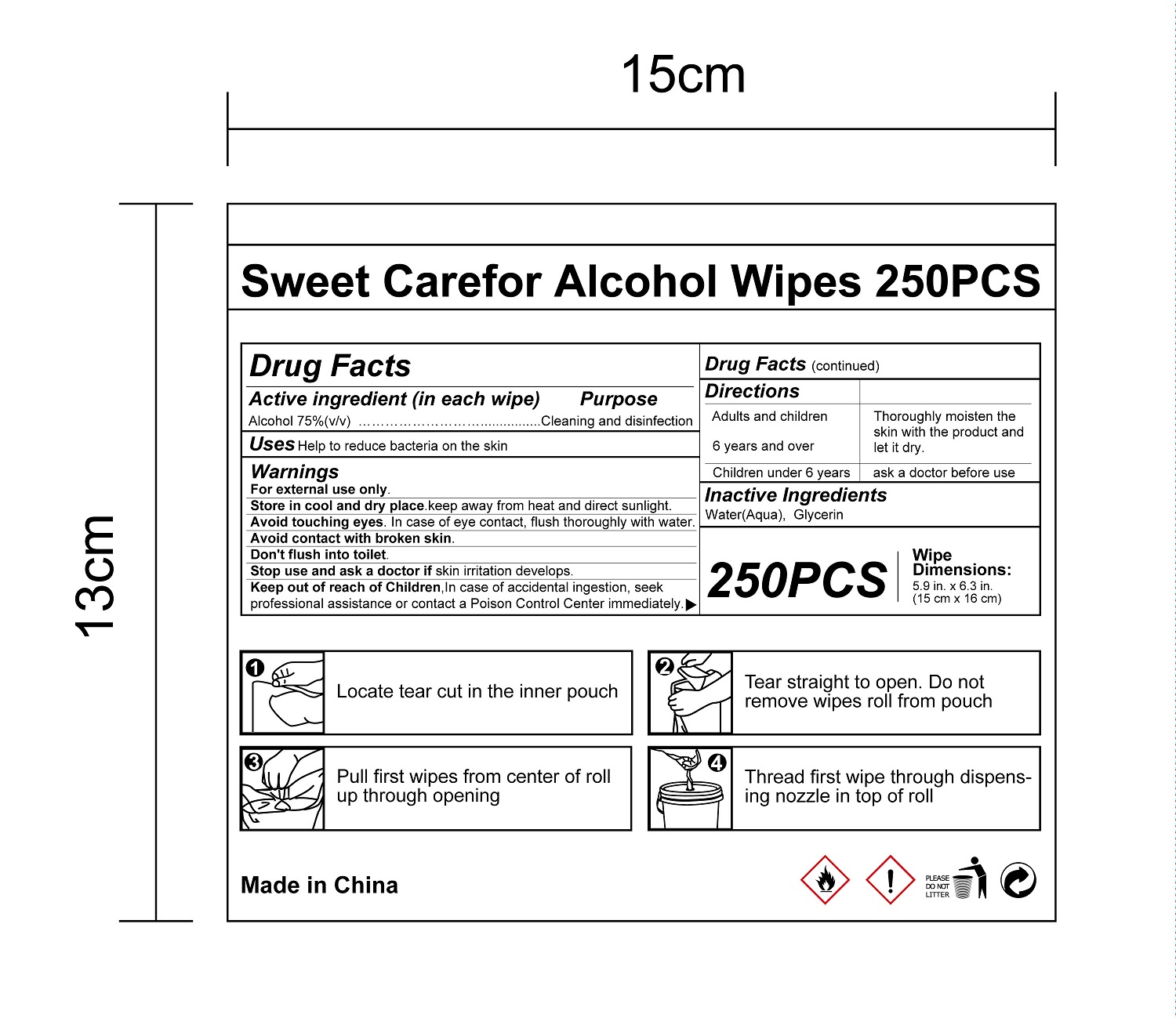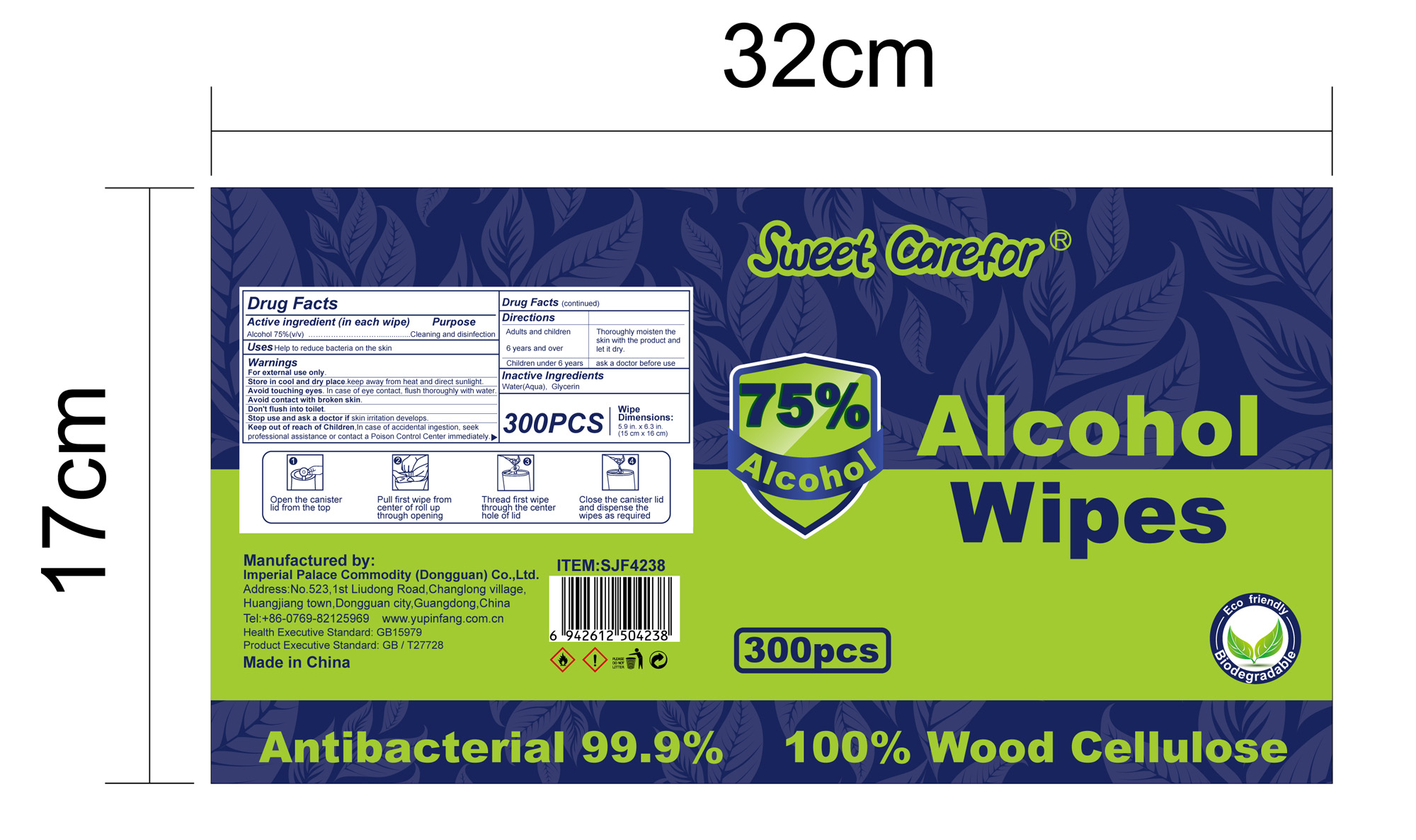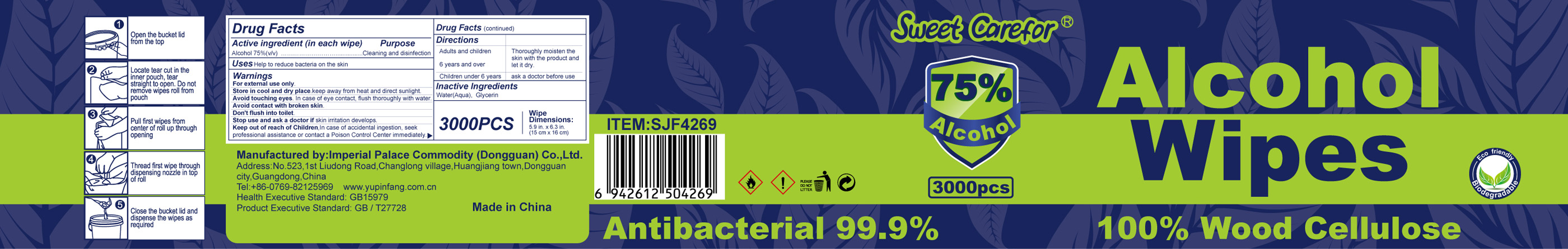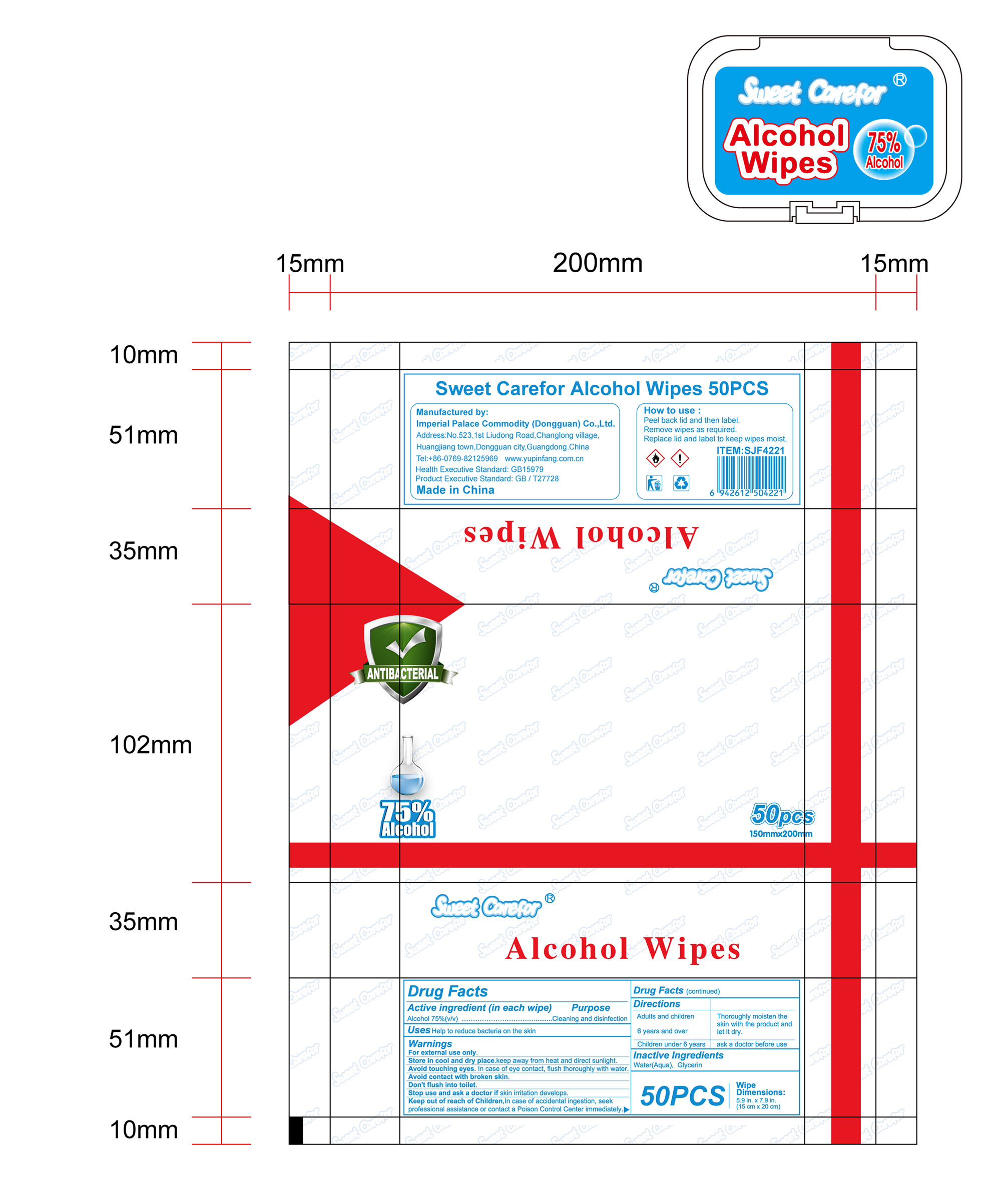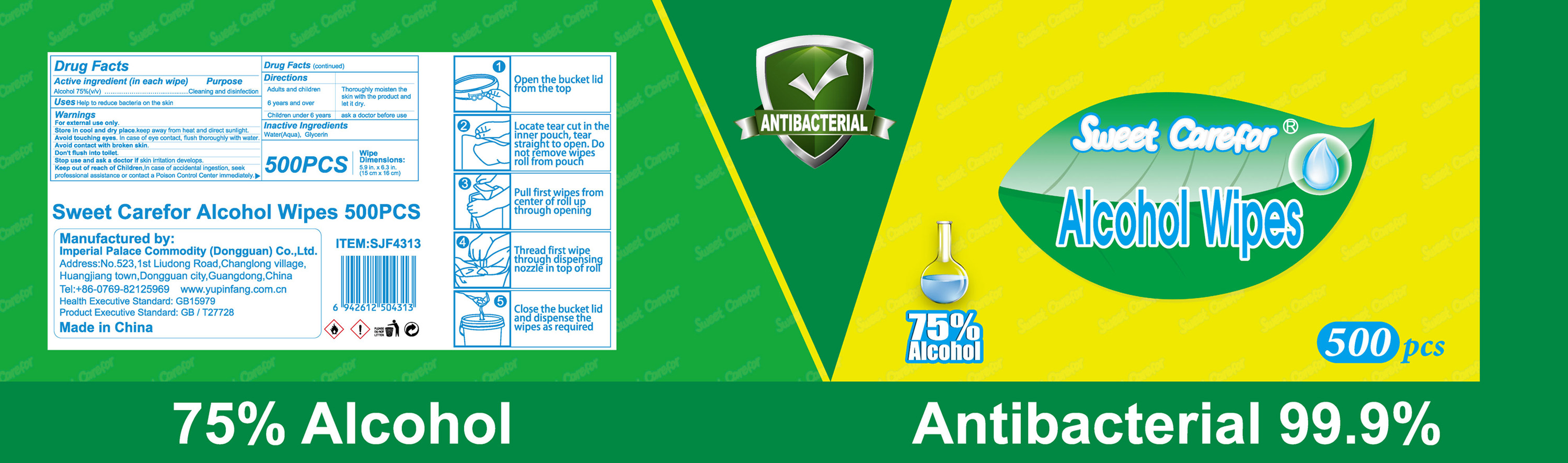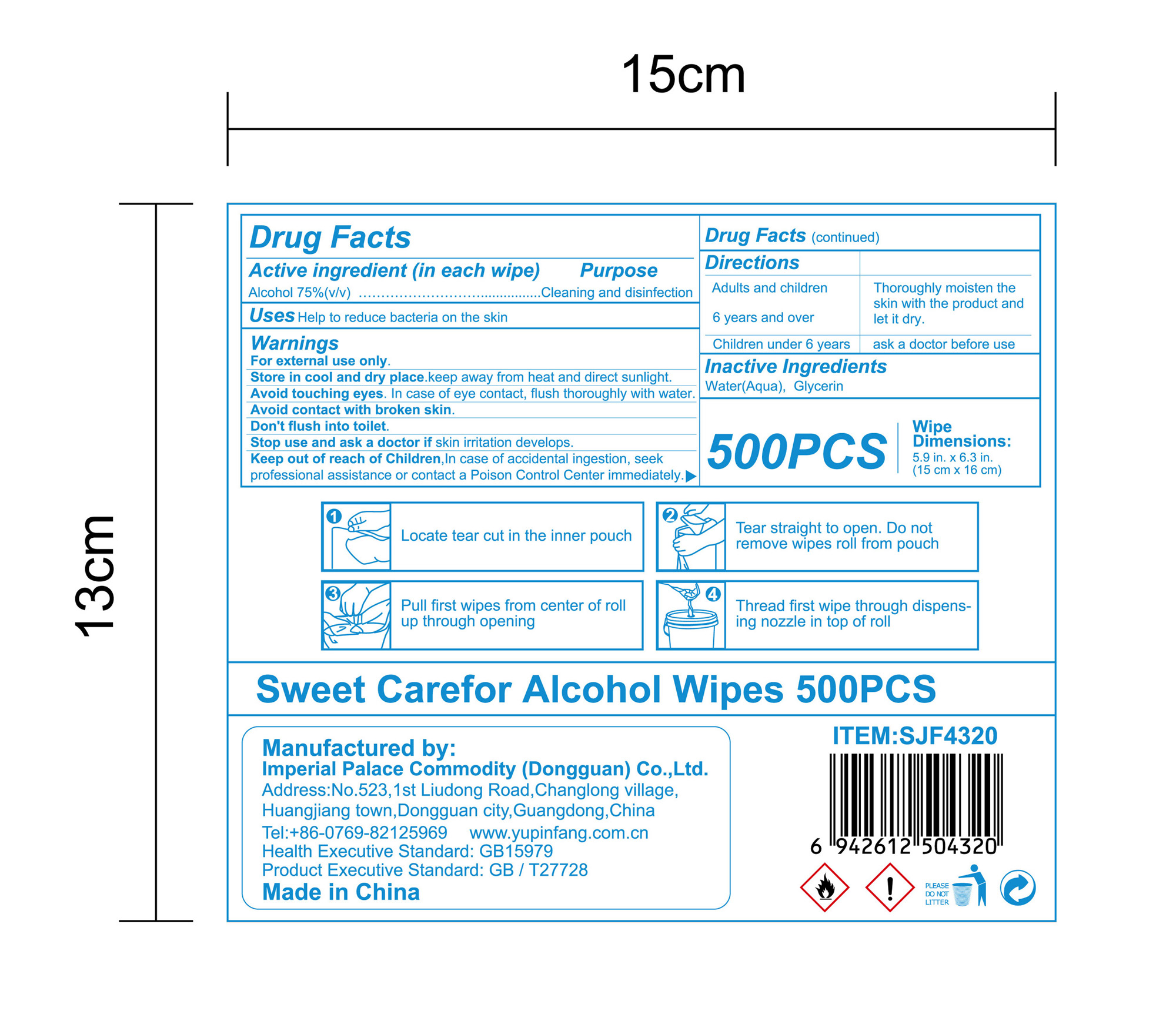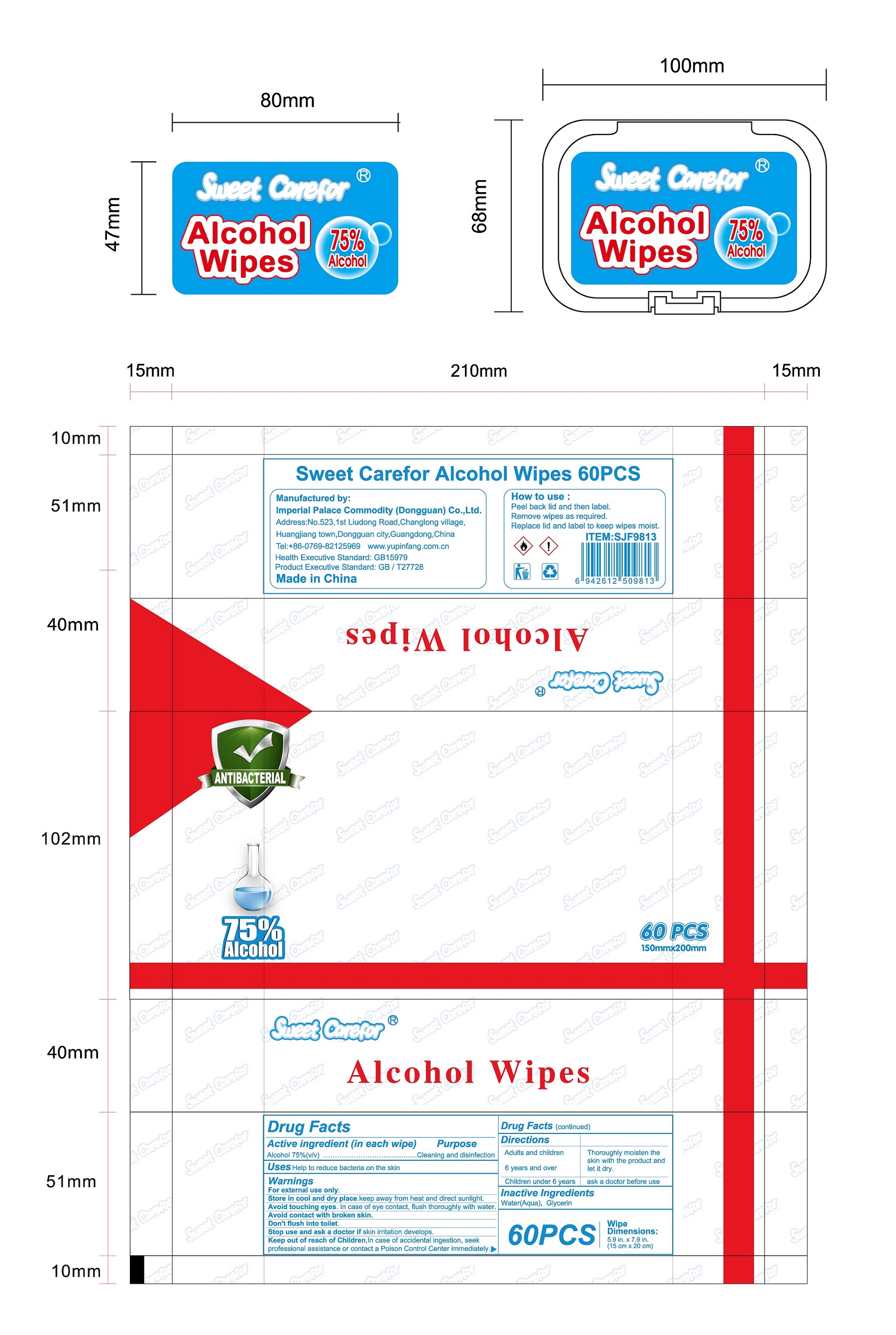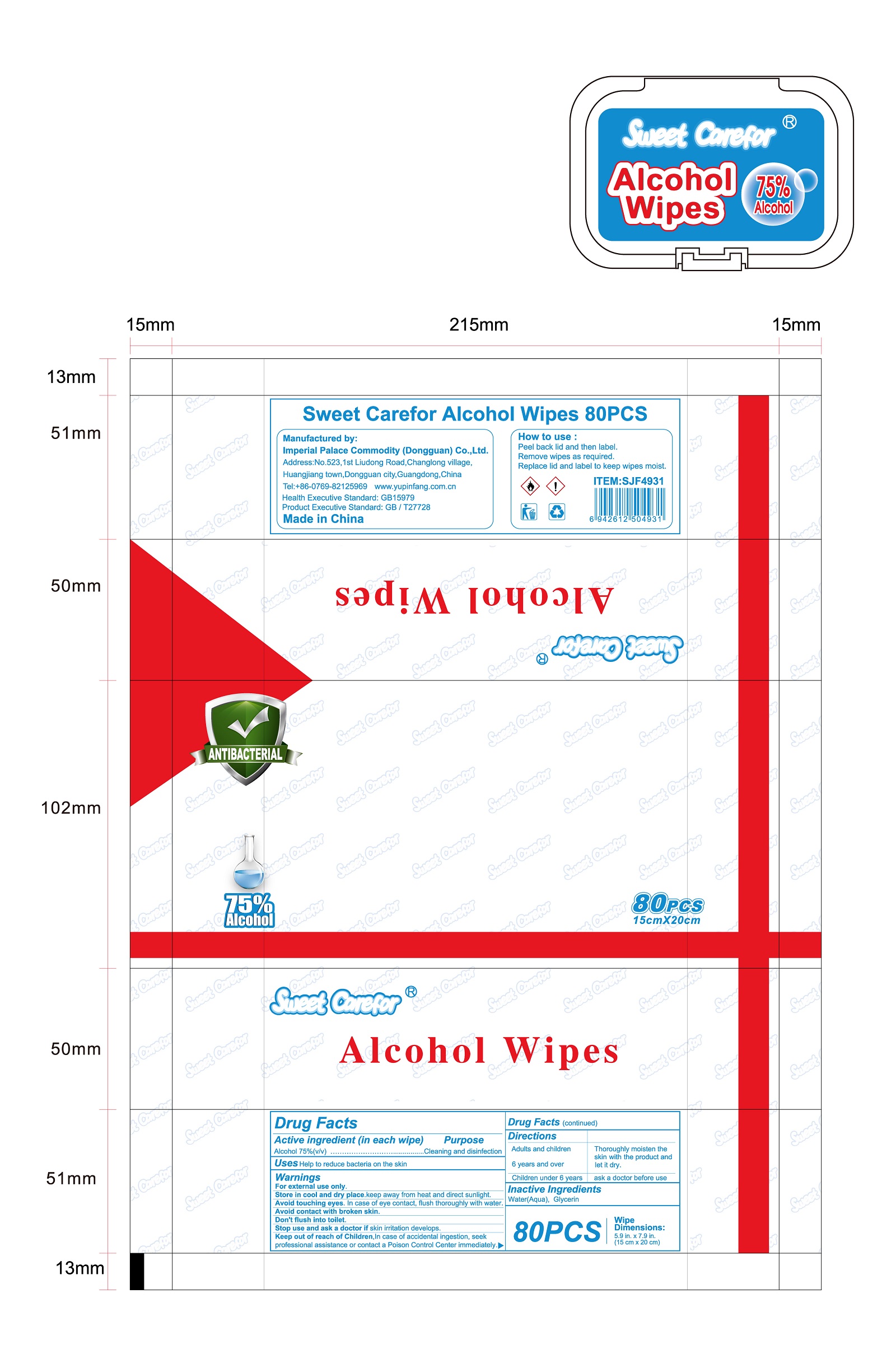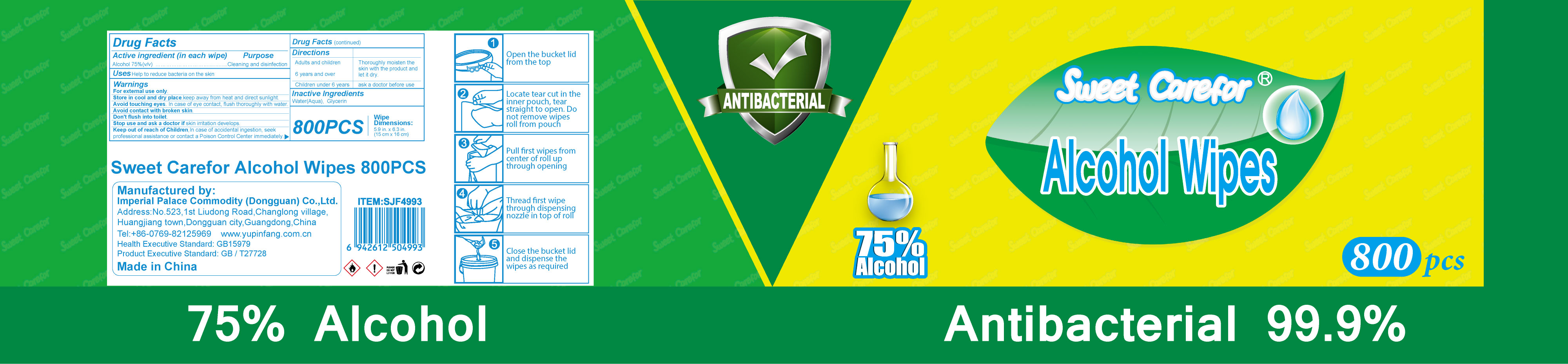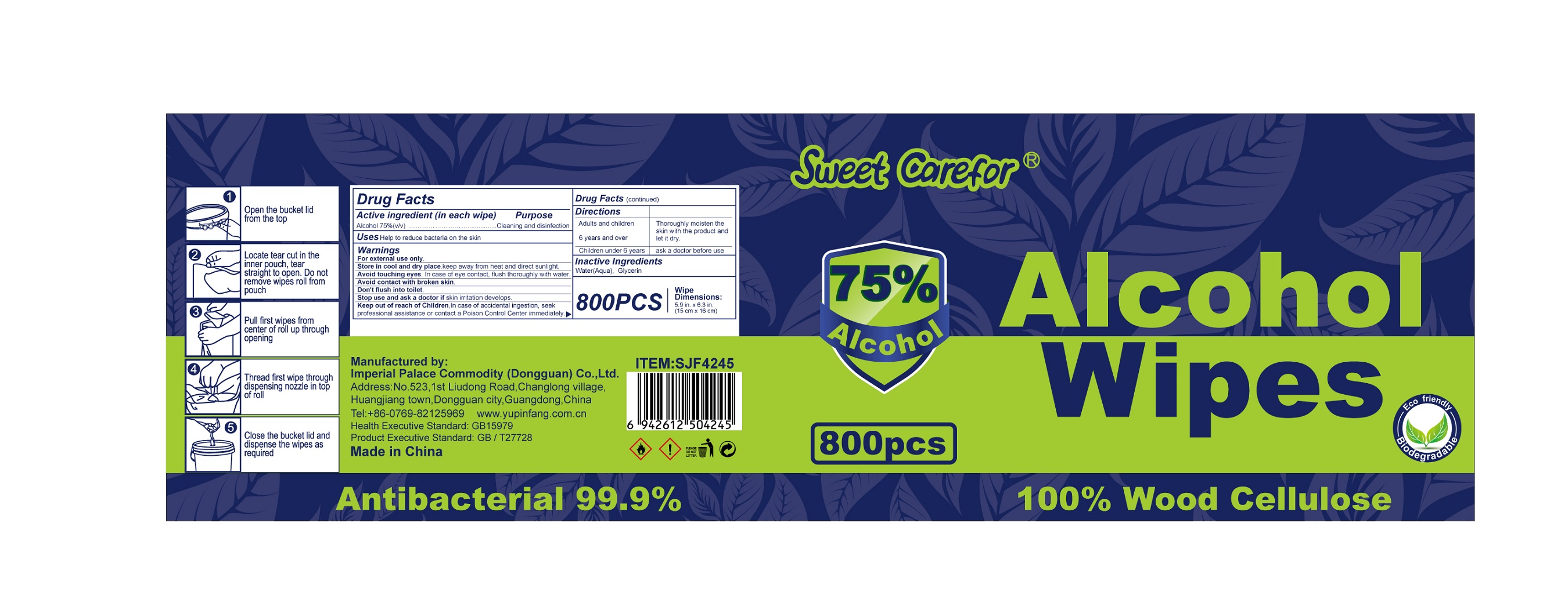 DRUG LABEL: Sweet Carefor Alcohol Wipes
NDC: 52489-001 | Form: CLOTH
Manufacturer: Imperial Palace Commodity(shenzhen)CO.,LTD
Category: otc | Type: HUMAN OTC DRUG LABEL
Date: 20231120

ACTIVE INGREDIENTS: ALCOHOL 75 mL/100 mL
INACTIVE INGREDIENTS: GLYCERIN; WATER

Sweet Carefor Alcohol Wipes

DRUG FACTS

Active Ingredient(s)

- Alcohol 75% v/v.

Purpose

- Cleaning and disinfection

Uses

Packs

- Peel back lid and then label.
- Remove wipes as required.
- Replace lid and label to keep wipes moist.

Buckets

- Open the bucket lid from the top.
- Locate tear cut in the inner pouch, tear straight to open. Do not remove wipesroll from pouch.
- Pull first wipes from center of roll up through opening.
- Thread first wipe through dispensing nozzle in top of roll.
- Close the bucket lid and dispense the wipes as required.

Warnings

- For external use only.
- Store in cool and dry place.keep away from heat and direct sunlight.
- Avoid touching eyes. In case of eye contact, flush thoroughly with water.
- Avoid contact with broken skin.
- Don't flush into toilet.
- Stop use and ask a doctor if skin irritation develops.

KEEP OUT OF REACH OF CHILDREN

- In case of accidental ingestion, seekprofessional assistance or contact a Poison Control Center immediately.

Directions

- Thoroughly moisten the skin or solid surface with the product and let it dry without wiping
- For children under 6, use only under adult supervision.
- Not recommended for infants.

Inactive ingredients

- Water, Glycerin

Package Label - Principal Display Panel

53 mL NDC: 52489-001-01

285 mL NDC: 52489-001-02

1020 mL NDC: 52489-001-03

3025 mL NDC: 52489-001-04

3.6 mL NDC: 52489-001-05

4.8 mL NDC: 52489-001-06

350 mL NDC: 52489-001-07

350 mL NDC: 52489-001-08

135ml NDC:52489-001-09

265ml NDC:52489-001-10

535ml NDC:52489-001-11

720ml NDC:52489-001-12

2140ml NDC:52489-001-13

1910ml NDC:52489-001-14

4760ml NDC:52489-001-15

7140ml NDC:52489-001-16

280 mL NDC: 52489-001-17

560 mL NDC: 52489-001-18

1020 mL NDC: 52489-001-19